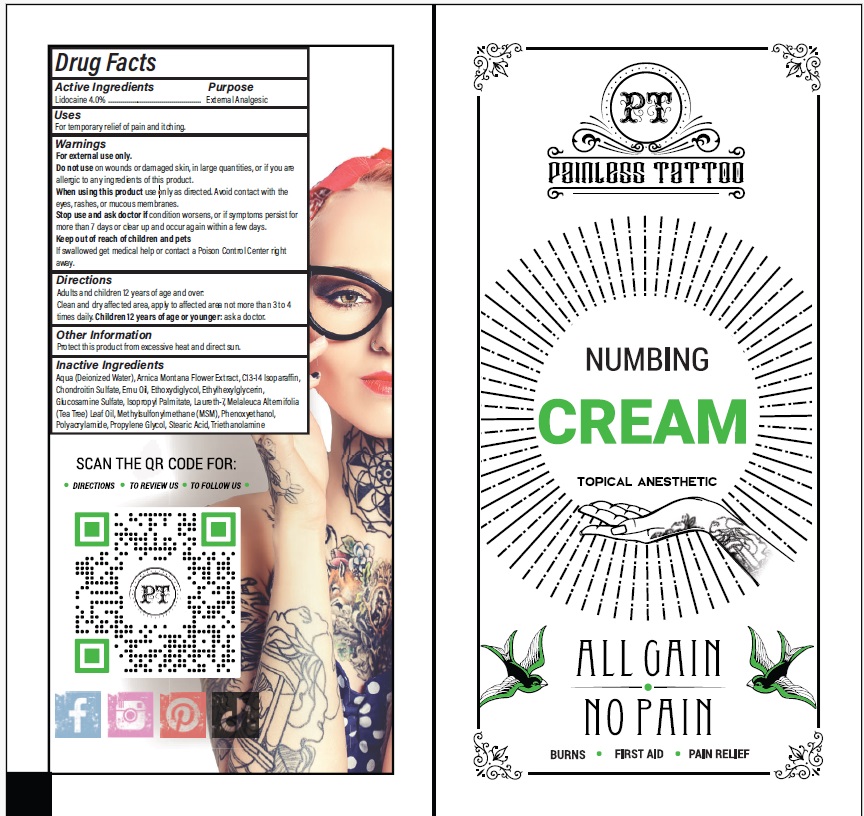 DRUG LABEL: Painless Tattoo Numbing Cream
NDC: 54723-020 | Form: CREAM
Manufacturer: Sambria Pharmaceuticals, LLC
Category: otc | Type: HUMAN OTC DRUG LABEL
Date: 20251112

ACTIVE INGREDIENTS: LIDOCAINE HYDROCHLORIDE 4 g/100 mL
INACTIVE INGREDIENTS: ARNICA MONTANA FLOWER; C13-14 ISOPARAFFIN; DIMETHYL SULFONE; EMU OIL; DIETHYLENE GLYCOL MONOETHYL ETHER; ETHYLHEXYLGLYCERIN; GLUCOSAMINE SULFATE; ISOPROPYL PALMITATE; LAURETH-7; TEA TREE OIL; PHENOXYETHANOL; POLYACRYLAMIDE (10000 MW); PROPYLENE GLYCOL; CHONDROITIN SULFATE (PORCINE; 5500 MW); STEARIC ACID; TROLAMINE; WATER

Active ingredient

Lidocaine HCL 4.0%

Purpose

External Analgesic

Uses

For temporary relief of pain and itching.

Warnings

For external use only.

Do not useon wounds or damaged skin, in large quantities, or if you are allergic to any ingredients of this product.

When using this productuse only as directed. Avoid contact with the eyes, rashes or mucous membranes.

Stop use and ask doctor ifcondition worsens, or if symptoms persist for more than 7 days or clear up and occur again within a few days.

Keep out of reach of childrenand pets If swallowed get medical help or contact a Poison Control Center right away.

Directions

Adults and children 12 years of age and over: Clean and dry affected area, apply to affected area not more than 3 to 4 times daily. Children 12 years of age or younger: ask a doctor.

Other Information

Protect this product from excessive heat and direct sun.

Inactive Ingredients

Aqua (Deionized Water), Arnica Montana Flower Extract, C13-14 Isoparaffin, Chondroitin Sulfate, Emu Oil, Ethoxydiglycol, Ethylhexylglycerin, Glucosamine Sulfate, Isopropyl Palmitate, Laureth-7, Melaleuca Alternifolia (Tea Tree) Leaf Oil, Methylsulfonylmethane (MSM), Phenoxyethanol, Polyacrylamide, Propylene Glycol, Stearic Acid, Triethanolamine